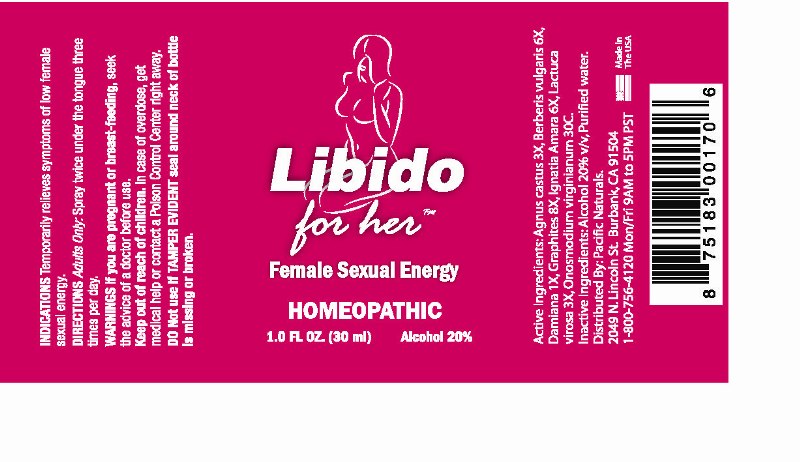 DRUG LABEL: Libido for Her
NDC: 43695-0001 | Form: SPRAY
Manufacturer: Pacific Naturals
Category: homeopathic | Type: HUMAN OTC DRUG LABEL
Date: 20120425

ACTIVE INGREDIENTS: CHASTE TREE 3 [hp_X]/1 mL; BERBERIS VULGARIS ROOT BARK 6 [hp_X]/1 mL; TURNERA DIFFUSA LEAFY TWIG 1 [hp_X]/1 mL; GRAPHITE 8 [hp_X]/1 mL; STRYCHNOS IGNATII SEED 6 [hp_X]/1 mL; LACTUCA VIROSA 3 [hp_X]/1 mL; ONOSMODIUM VIRGINIANUM WHOLE 30 [hp_C]/1 mL
INACTIVE INGREDIENTS: ALCOHOL; WATER

Libido for Her

ACTIVE INGREDIENT

ACTIVE INGREDIENTS: Agnus castus 3X, Berberis vulgaris 6X, Damiana 1X, Graphites 8X, Ignatia amara 6X, Lactuca virosa 3X, Onosmodium virginianum 30C.

PURPOSE

INDICATIONS: Temporarily relieves symptoms of low female sexual energy.

WARNINGS

WARNINGS: If you are pregnant or breast-feeding, seek the advice of a doctor before use.

Keep out of reach of children. In case of overdose, get medical help or contact a Poison Control Center right away.

Do Not use if TAMPER EVIDENT seal around neck of bottle is missing or broken.

DOSAGE AND ADMINISTRATION

DIRECTIONS: Adults Only: Spray twice under the tongue three times per day.

INACTIVE INGREDIENTS: Alcohol 20% v/v, Purified Water.

KEEP OUT OF REACH OF CHILDREN. In case of overdose, get medical help or contact a Poison Control Center right away.

INDICATIONS AND USAGE

INDICATIONS: Temporarily relieves symptoms of low female sexual energy.

QUESTIONS

Distributed By:

Pacific Naturals

2049 N. Lincoln St

Burbank, CA 91504

1-800-756-4120 Mon/Fri 9AM to 5PM PST

PACKAGE LABEL

Libido for her

Female Sexual Energy

HOMEOPATHIC

1.0 FL OZ (30 ml)